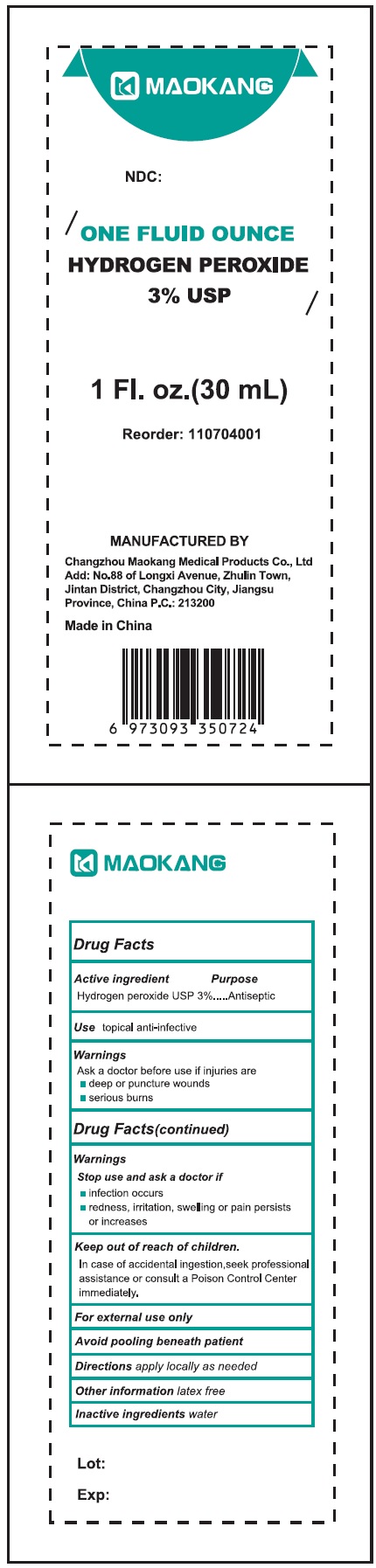 DRUG LABEL: Maokang 3 Hydrogen Peroxide
NDC: 59050-268 | Form: SOLUTION
Manufacturer: Changzhou Maokang Medical Products Co., Ltd
Category: otc | Type: HUMAN OTC DRUG LABEL
Date: 20231109

ACTIVE INGREDIENTS: HYDROGEN PEROXIDE 30 mg/1 mL
INACTIVE INGREDIENTS: WATER

Maokang 3% Hydrogen Peroxide

Active ingredient

Hydrogen peroxide USP 3%

Purpose

Antiseptic

Use

topical anti-infective

Warnings

Ask a doctor before use if injuries are

- deep or puncture wounds
- serious burns

Stop use and ask a doctor if

- infection occurs
- redness, irritation, swelling or pain persists or increases

Keep out of reach of children.

In case of accidental ingestion,seek professional assistance or consult a Poison Control Center immediately.

For external use only

Avoid pooling beneath patient

Directions

apply locally as needed

Other information

latex free

Inactive ingredients

water